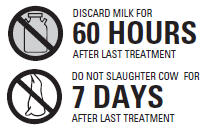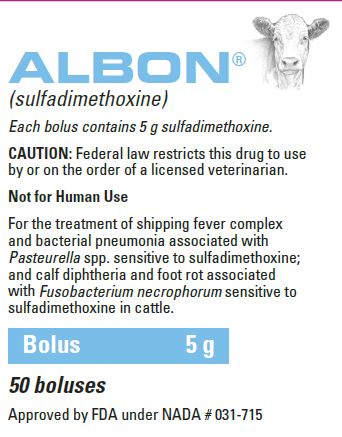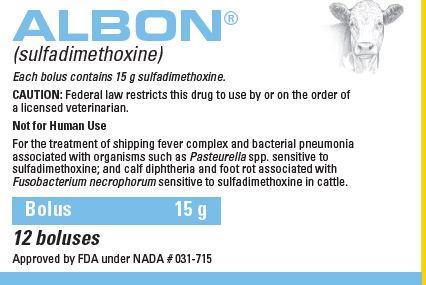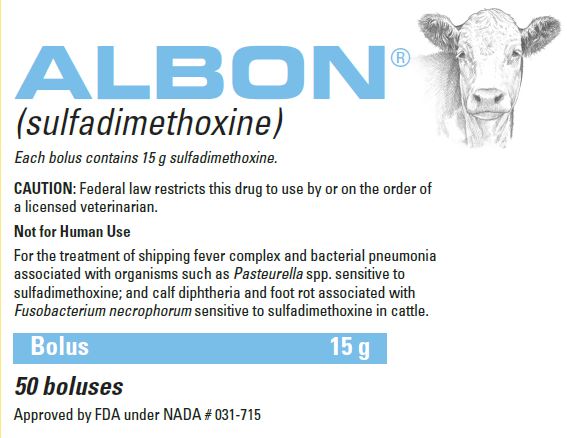 DRUG LABEL: Albon
NDC: 54771-8449 | Form: TABLET
Manufacturer: Zoetis Inc.
Category: animal | Type: PRESCRIPTION ANIMAL DRUG LABEL
Date: 20230608

ACTIVE INGREDIENTS: sulfadimethoxine 5 g/1 1

ALBON® Boluses

ALBON®
(sulfadimethoxine)
Boluses

CAUTION

Federal law restricts this drug to use by or on the order of a licensed veterinarian.

DESCRIPTION

Albon is a low-dose, rapidly absorbed, long-acting sulfonamide.

Actions

Sulfadimethoxine has been demonstrated in laboratory studies to be effective against a wide variety of organisms, such as streptococci, staphylococci, and members of the E. coli-salmonella group of bacteria.
Comparatively low doses of Albon give rapid, sustained blood levels required for effective disease therapy.

INDICATIONS AND USAGE

Albon is effective in the treatment of shipping fever complex and bacterial pneumonia associated with Pasteurella spp. sensitive to sulfadimethoxine; and calf diphtheria and foot rot associated with Fusobacterium necrophorum sensitive to sulfadimethoxine in cattle.

WARNINGS

Not for Human Use

Milk taken from animals during treatment and for 60 hours (5 milkings) after the latest treatment must not be used for food.

Do not slaughter animals for food purposes within 7 days following the last treatment.

A withdrawal period has not been established for this product in preruminating calves.

Do Not Use in Calves to be Processed for Veal

PRECAUTIONS

During treatment period, make certain that animals maintain adequate water intake.

If animals show no improvement within 2–3 days, reevaluate your diagnosis. Treatment should not be continued beyond 5 days.

DOSAGE AND ADMINISTRATION

Albon should be administered to cattle so that the initial dose is equivalent to 25 mg/lb of body weight and each subsequent daily dose is equivalent to 12.5 mg/lb of body weight. Length of treatment will depend on clinical response. In most cases, treatment for 3–4 days is adequate. Treatment should not be continued beyond 5 days.

The following tables show the dosage and dosage forms to be used for cattle of different weights.

Albon Boluses, 5 g

Dosage Schedule for Cattle: 200–600 lb of body weight

Animal Weight, lb | First Day | Daily for the Following 3–4 Days
200 | 1 bolus | 1/2 bolus
300 | 1 1/2 boluses | 1 bolus
400 | 2 boluses | 1 bolus
500 | 2 1/2 boluses | 1 1/2 boluses
600 | 3 boluses | 1 1/2 boluses

Albon Boluses, 15 g

Dosage Schedule for Cattle: 600–1,200 lb of body weight

Animal Weight, lb | First Day | Daily for the Following 3–4 Days
600 | 1 bolus | 1/2 bolus
800 | 1 1/2 boluses | 1 bolus
1,000-1,200 | 2 boluses | 1 bolus

TOXICITY AND SAFETY

Albon has been shown to be a well-tolerated sulfonamide with relatively high solubility at the pH normally occurring in the kidney and with a low degree of tox- icity. Following the administration of Albon at the recommended dosage, no undesirable side effects have been observed.

STORAGE AND HANDLING

Store at Controlled Room Temperature 15°–30°C (59°–86°F)

HOW SUPPLIED

Albon Boluses are supplied in the following dosage forms:

5 g sulfadimethoxine per single-scored bolus

15 g sulfadimethoxine per single-scored bolus

Approved by FDA under NADA # 031-715

zoetis

Distributed by:
Zoetis Inc.
Kalamazoo, MI 49007

40039314
Revised: June 2022